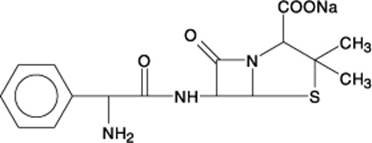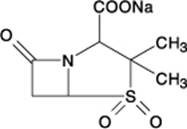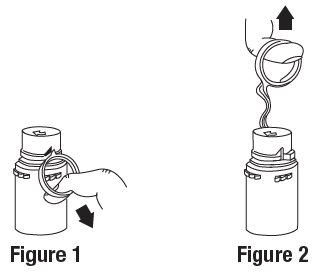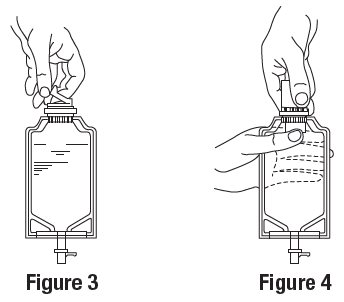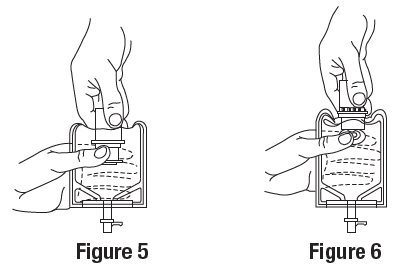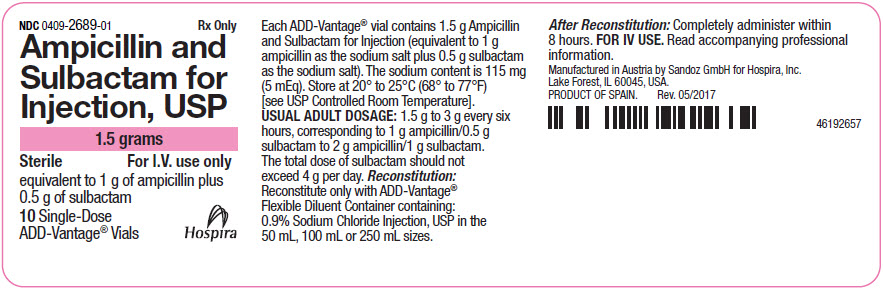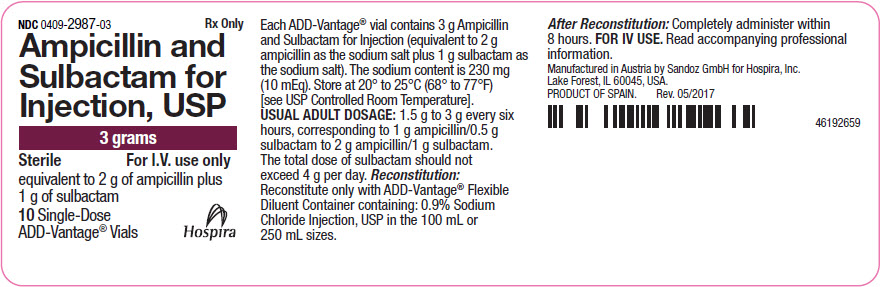 DRUG LABEL: Ampicillin and Sulbactam
NDC: 0409-2689 | Form: INJECTION, POWDER, FOR SOLUTION
Manufacturer: Hospira, Inc
Category: prescription | Type: HUMAN PRESCRIPTION DRUG LABEL
Date: 20260121

ACTIVE INGREDIENTS: AMPICILLIN SODIUM 1 g/1 1; SULBACTAM SODIUM 0.5 g/1 1

Ampicillin and Sulbactam for Injection, USP

ADD-Vantage® Vials

Rx Only

To reduce the development of drug-resistant bacteria and maintain the effectiveness of Ampicillin and Sulbactam for Injection and other antibacterial drugs, Ampicillin and Sulbactam for Injection should be used only to treat infections that are proven or strongly suspected to be caused by bacteria.

DESCRIPTION

Ampicillin and sulbactam for injection, USP is a sterile antibacterial fixed-combination drug product consisting of the semisynthetic antibacterial ampicillin sodium and the beta-lactamase inhibitor sulbactam sodium for intravenous administration.

Ampicillin sodium is derived from the penicillin nucleus, 6-aminopenicillanic acid. Chemically, it is monosodium (2S, 5R, 6R)-6-[(R)-2-amino-2-phenylacetamido]-3,3-dimethyl-7-oxo-4-thia-1-azabicyclo[3.2.0]heptane-2-carboxylate and has a molecular weight of 371.39. Its chemical formula is C16H18N3NaO4S.

The structural formula is:

Sulbactam sodium is a derivative of the basic penicillin nucleus. Chemically, sulbactam sodium is sodium penicillinate sulfone; sodium (2S, 5R)-3,3-dimethyl-7-oxo-4-thia-1-azabicyclo[3.2.0]heptane-2-carboxylate 4,4-dioxide. Its chemical formula is C8H10NNaO5S with a molecular weight of 255.22.

The structural formula is:

Ampicillin and sulbactam for injection, USP parenteral combination, is available as a white to yellowish dry powder for reconstitution. Ampicillin and sulbactam for injection, USP dry powder is freely soluble in aqueous diluents to yield pale yellow to yellow solutions containing ampicillin sodium and sulbactam sodium equivalent to 250 mg ampicillin per mL and 125 mg sulbactam per mL. The pH of the solutions is between 8 and 10.

Dilute solutions (up to 30 mg ampicillin and 15 mg sulbactam per mL) are essentially colorless to pale yellow. The pH of dilute solutions remains the same.

Each 1.5 g ADD-Vantage® vial contains 1.5 g ampicillin and sulbactam for injection, USP (equivalent to 1 g ampicillin as the sodium salt plus 0.5 g sulbactam as the sodium salt). The sodium content is 115 mg (5 mEq).

Each 3 g ADD-Vantage® vial contains 3 g ampicillin and sulbactam for injection, USP (equivalent to 2 g ampicillin as the sodium salt plus 1 g sulbactam as the sodium salt). The sodium content is 230 mg (10 mEq).

CLINICAL PHARMACOLOGY

General

Immediately after completion of a 15-minute intravenous infusion of ampicillin and sulbactam, peak serum concentrations of ampicillin and sulbactam are attained. Ampicillin serum levels are similar to those produced by the administration of equivalent amounts of ampicillin alone. Peak ampicillin serum levels ranging from 109 to 150 mcg/mL are attained after administration of 2000 mg of ampicillin plus 1000 mg sulbactam and 40 to 71 mcg/mL after administration of 1000 mg ampicillin plus 500 mg sulbactam. The corresponding mean peak serum levels for sulbactam range from 48 to 88 mcg/mL and 21 to 40 mcg/mL, respectively.

The mean serum half-life of both drugs is approximately 1 hour in healthy volunteers.

Approximately 75 to 85% of both ampicillin and sulbactam are excreted unchanged in the urine during the first 8 hours after administration of ampicillin and sulbactam to individuals with normal renal function. Somewhat higher and more prolonged serum levels of ampicillin and sulbactam can be achieved with the concurrent administration of probenecid.

In patients with impaired renal function the elimination kinetics of ampicillin and sulbactam are similarly affected, hence the ratio of one to the other will remain constant whatever the renal function. The dose of ampicillin and sulbactam for injection in such patients should be administered less frequently in accordance with the usual practice for ampicillin (see DOSAGE and ADMINISTRATION section).

Ampicillin has been found to be approximately 28% reversibly bound to human serum protein and sulbactam approximately 38% reversibly bound.

The following average levels of ampicillin and sulbactam were measured in the tissues and fluids listed:

TABLE 1: Concentration of Ampicillin and Sulbactam for Injection in Various Body Tissues and Fluids

Fluid or Tissue | Dose (grams) Ampicillin/Sulbactam | Concentration (mcg/mL or mcg/g) Ampicillin/Sulbactam
Peritoneal Fluid | 0.5/0.5 IV | 7/14
Blister Fluid (Cantharides) | 0.5/0.5 IV | 8/20
Tissue Fluid | 1/0.5 IV | 8/4
Intestinal Mucosa | 0.5/0.5 IV | 11/18
Appendix | 2/1 IV | 3/40

Penetration of both ampicillin and sulbactam into cerebrospinal fluid in the presence of inflamed meninges has been demonstrated after IV administration of ampicillin and sulbactam.

The pharmacokinetics of ampicillin and sulbactam in pediatric patients receiving ampicillin and sulbactam are similar to those observed in adults. Immediately after a 15-minute infusion of 50 to 75 mg ampicillin and sulbactam/kg body weight, peak serum and plasma concentrations of 82 to 446 mcg ampicillin/mL and 44 to 203 mcg sulbactam/mL were obtained. Mean half-life values were approximately 1 hour.

MICROBIOLOGY

Mechanism of Action

Ampicillin is similar to benzyl penicillin in its bactericidal action against susceptible organisms during the stage of active multiplication. It acts through the inhibition of cell wall mucopeptide biosynthesis. Ampicillin has a broad spectrum of bactericidal activity against many gram-positive and gram-negative aerobic and anaerobic bacteria. (Ampicillin is, however, degraded by beta-lactamases and therefore the spectrum of activity does not normally include organisms which produce these enzymes).

A wide range of beta-lactamases found in microorganisms resistant to penicillins and cephalosporins have been shown in biochemical studies with cell free bacterial systems to be irreversibly inhibited by sulbactam. Although sulbactam alone possesses little useful antibacterial activity except against the Neisseriaceae, whole organism studies have shown that sulbactam restores ampicillin activity against beta-lactamase producing strains. In particular, sulbactam has good inhibitory activity against the clinically important plasmid mediated beta-lactamases most frequently responsible for transferred drug resistance. Sulbactam has no effect on the activity of ampicillin against ampicillin-susceptible strains.

The presence of sulbactam in the ampicillin and sulbactam for injection formulation effectively extends the antibacterial spectrum of ampicillin to include many bacteria normally resistant to it and to other beta-lactam antibacterials. Thus, ampicillin and sulbactam possesses the properties of a broad-spectrum antibacterial and a beta-lactamase inhibitor.

Antimicrobial Activity

While in vitro studies have demonstrated the susceptibility of most strains of the following organisms, clinical efficacy for infections other than those included in the INDICATIONS and USAGE section has not been documented.

Gram-positive Bacteria:

Staphylococcus aureus (beta-lactamase and non-beta-lactamase producing)

Staphylococcus epidermidis (beta-lactamase and non-beta-lactamase producing)

Staphylococcus saprophyticus (beta-lactamase and non-beta-lactamase producing)

Enterococcus faecalis†

Streptococcus pneumoniae†

Streptococcus pyogenes†

Streptococcus viridans†

Gram-negative Bacteria:

Hemophilus influenzae (beta-lactamase and non-beta-lactamase producing)

Moraxella catarrhalis (beta-lactamase and non-beta-lactamase producing)

Escherichia coli (beta-lactamase and non-beta-lactamase producing)

Klebsiella species (all known strains are beta-lactamase producing)

Proteus mirabilis (beta-lactamase and non-beta-lactamase producing)

Proteus vulgaris

Providencia rettgeri

Providencia stuartii

Morganella morganii

Neisseria gonorrhoeae (beta-lactamase and non-beta-lactamase producing)

Anaerobes:

Clostridium species†

Peptococcus species†

Peptostreptococcus species

Bacteroides species, including B. fragilis

†These are not beta-lactamase producing strains and, therefore, are susceptible to ampicillin alone.

Susceptibility Testing

For specific information regarding susceptibility test interpretive criteria and associated test methods and quality control standards recognized by FDA for this drug, please see: https://www.fda.gov/STIC.

INDICATIONS AND USAGE

Ampicillin and sulbactam for injection is indicated for the treatment of infections due to susceptible strains of the designated microorganisms in the conditions listed below.

Skin and Skin Structure Infections caused by beta-lactamase producing strains of Staphylococcus aureus, Escherichia coli,* Klebsiella spp.* (including K. pneumoniae*), Proteus mirabilis,* Bacteroides fragilis,* Enterobacter spp.,* and Acinetobacter calcoaceticus.*

NOTE: For information on use in pediatric patients (see PRECAUTIONS - Pediatric Use and CLINICAL STUDIES sections).

Intra-Abdominal Infections caused by beta-lactamase producing strains of Escherichia coli, Klebsiella spp. (including K. pneumoniae*), Bacteroides spp. (including B. fragilis), and Enterobacter spp.*

Gynecological Infections caused by beta-lactamase producing strains of Escherichia coli,* and Bacteroides spp.* (including B. fragilis*).

* Efficacy for this organism in this organ system was studied in fewer than 10 infections.

While ampicillin and sulbactam for injection is indicated only for the conditions listed above, infections caused by ampicillin-susceptible organisms are also amenable to treatment with ampicillin and sulbactam for injection due to its ampicillin content. Therefore, mixed infections caused by ampicillin-susceptible organisms and beta-lactamase producing organisms susceptible to ampicillin and sulbactam for injection should not require the addition of another antibacterial.

Appropriate culture and susceptibility tests should be performed before treatment in order to isolate and identify the organisms causing infection and to determine their susceptibility to ampicillin and sulbactam for injection.

Therapy may be instituted prior to obtaining the results from bacteriological and susceptibility studies when there is reason to believe the infection may involve any of the beta-lactamase producing organisms listed above in the indicated organ systems. Once the results are known, therapy should be adjusted if appropriate.

To reduce the development of drug-resistant bacteria and maintain effectiveness of ampicillin and sulbactam for injection and other antibacterial drugs, ampicillin and sulbactam for injection should be used only to treat infections that are proven or strongly suspected to be caused by susceptible bacteria. When culture and susceptibility information are available, they should be considered in selecting or modifying antibacterial therapy. In the absence of such data, local epidemiology and susceptibility patterns may contribute to the empiric selection of therapy.

CONTRAINDICATIONS

The use of ampicillin and sulbactam for injection is contraindicated in individuals with a history of serious hypersensitivity reactions (e.g., anaphylaxis or Stevens-Johnson syndrome) to ampicillin, sulbactam or to other beta-lactam antibacterial drugs (e.g., penicillins and cephalosporins).

Ampicillin and sulbactam for injection is contraindicated in patients with a previous history of cholestatic jaundice/hepatic dysfunction associated with ampicillin and sulbactam for injection.

WARNINGS

Hypersensitivity

Serious and occasionally fatal hypersensitivity (anaphylactic) reactions have been reported in patients on penicillin therapy. These reactions are more apt to occur in individuals with a history of penicillin hypersensitivity and/or hypersensitivity reactions to multiple allergens. There have been reports of individuals with a history of penicillin hypersensitivity who have experienced severe reactions when treated with cephalosporins. Before therapy with a penicillin, careful inquiry should be made concerning previous hypersensitivity reactions to penicillins, cephalosporins, and other allergens. If an allergic reaction occurs, ampicillin and sulbactam for injection should be discontinued and the appropriate therapy instituted.

Hepatotoxicity

Hepatic dysfunction, including hepatitis and cholestatic jaundice has been associated with the use of ampicillin and sulbactam for injection. Hepatic toxicity is usually reversible; however, deaths have been reported. Hepatic function should be monitored at regular intervals in patients with hepatic impairment.

Severe Cutaneous Adverse Reactions

Ampicillin and sulbactam for injection may cause severe skin reactions, such as toxic epidermal necrolysis (TEN), Stevens-Johnson syndrome (SJS), drug reaction with eosinophilia and systemic symptoms (DRESS), dermatitis exfoliative, erythema multiforme, and Acute generalized exanthematous pustulosis (AGEP). If patients develop a skin rash they should be monitored closely and ampicillin and sulbactam for injection discontinued if lesions progress (see CONTRAINDICATIONS and ADVERSE REACTIONS sections).

Clostridioides difficile-associated diarrhea (CDAD) has been reported with use of nearly all antibacterial agents, including ampicillin and sulbactam for injection, and may range in severity from mild diarrhea to fatal colitis. Treatment with antibacterial agents alters the normal flora of the colon leading to overgrowth of C. difficile.

C. difficile produces toxins A and B which contribute to the development of CDAD. Hypertoxin producing strains of C. difficile cause increased morbidity and mortality, as these infections can be refractory to antimicrobial therapy and may require colectomy. CDAD must be considered in all patients who present with diarrhea following antibacterial drug use. Careful medical history is necessary since CDAD has been reported to occur over two months after the administration of antibacterial agents.

If CDAD is suspected or confirmed, ongoing antibacterial drug use not directed against C. difficile may need to be discontinued. Appropriate fluid and electrolyte management, protein supplementation, antibacterial treatment of C. difficile, and surgical evaluation should be instituted as clinically indicated.

PRECAUTIONS

General

A high percentage of patients with mononucleosis who receive ampicillin develop a skin rash. Thus, ampicillin class antibacterials should not be administered to patients with mononucleosis. In patients treated with ampicillin and sulbactam the possibility of superinfections with mycotic or bacterial pathogens should be kept in mind during therapy. If superinfections occur (usually involving Pseudomonas or Candida), the drug should be discontinued and/or appropriate therapy instituted.

Prescribing ampicillin and sulbactam for injection in the absence of proven or strongly suspected bacterial infection or a prophylactic indication is unlikely to provide benefit to the patient and increases the risk of the development of drug-resistant bacteria.

Information for Patients

Patients should be counseled that antibacterial drugs including ampicillin and sulbactam for injection should only be used to treat bacterial infections. They do not treat viral infections (e.g., the common cold). When ampicillin and sulbactam for injection is prescribed to treat a bacterial infection, patients should be told that although it is common to feel better early in the course of therapy, the medication should be taken exactly as directed. Skipping doses or not completing the full course of therapy may (1) decrease the effectiveness of the immediate treatment and (2) increase the likelihood that bacteria will develop resistance and will not be treatable by ampicillin and sulbactam for injection or other antibacterial drugs in the future.

Diarrhea is a common problem caused by antibacterials which usually ends when the antibacterial is discontinued. Sometimes after starting treatment with antibacterials, patients can develop watery and bloody stools (with or without stomach cramps and fever) even as late as two or more months after having taken the last dose of the antibacterial. If this occurs, patients should contact their physician as soon as possible.

Drug Interactions

Probenecid decreases the renal tubular secretion of ampicillin and sulbactam. Concurrent use of probenecid with ampicillin and sulbactam may result in increased and prolonged blood levels of ampicillin and sulbactam. The concurrent administration of allopurinol and ampicillin increases substantially the incidence of rashes in patients receiving both drugs as compared to patients receiving ampicillin alone. It is not known whether this potentiation of ampicillin rashes is due to allopurinol or the hyperuricemia present in these patients. There are no data with ampicillin and sulbactam and allopurinol administered concurrently. Ampicillin and sulbactam and aminoglycosides should not be reconstituted together due to the in vitro inactivation of aminoglycosides by the ampicillin component of ampicillin and sulbactam.

Drug/Laboratory Test Interactions

Administration of ampicillin and sulbactam will result in high urine concentration of ampicillin. High urine concentrations of ampicillin may result in false positive reactions when testing for the presence of glucose in urine using Clinitest™, Benedict's Solution or Fehling's Solution. It is recommended that glucose tests based on enzymatic glucose oxidase reactions (such as Clinistix™ or Testape™) be used. Following administration of ampicillin to pregnant women, a transient decrease in plasma concentration of total conjugated estriol, estriol-glucuronide, conjugated estrone and estradiol has been noted. This effect may also occur with ampicillin and sulbactam.

Carcinogenesis, Mutagenesis, Impairment of Fertility

Long-term studies in animals have not been performed to evaluate carcinogenic or mutagenic potential.

Pregnancy

Reproduction studies have been performed in mice, rats, and rabbits at doses up to ten (10) times the human dose and have revealed no evidence of impaired fertility or harm to the fetus due to ampicillin and sulbactam. There are, however, no adequate and well-controlled studies in pregnant women. Because animal reproduction studies are not always predictive of human response, this drug should be used during pregnancy only if clearly needed (see PRECAUTIONS - Drug/Laboratory Test Interactions section).

Labor and Delivery

Studies in guinea pigs have shown that intravenous administration of ampicillin decreased the uterine tone, frequency of contractions, height of contractions, and duration of contractions. However, it is not known whether the use of ampicillin and sulbactam in humans during labor or delivery has immediate or delayed adverse effects on the fetus, prolongs the duration of labor, or increases the likelihood that forceps delivery or other obstetrical intervention or resuscitation of the newborn will be necessary.

Nursing Mothers

Low concentrations of ampicillin and sulbactam are excreted in the milk; therefore, caution should be exercised when ampicillin and sulbactam is administered to a nursing woman.

Pediatric Use

The safety and effectiveness of ampicillin and sulbactam for injection have been established for pediatric patients one year of age and older for skin and skin structure infections as approved in adults. Use of ampicillin and sulbactam for injection in pediatric patients is supported by evidence from adequate and well-controlled studies in adults with additional data from pediatric pharmacokinetic studies, a controlled clinical trial conducted in pediatric patients and post-marketing adverse events surveillance (seeCLINICAL PHARMACOLOGY, INDICATIONS AND USAGE, ADVERSE REACTIONS, DOSAGE AND ADMINISTRATION, andCLINICAL STUDIESsections).

The safety and effectiveness of ampicillin and sulbactam for injection have not been established for pediatric patients for intra-abdominal infections.

ADVERSE REACTIONS

Adult Patients

Ampicillin and sulbactam for injection is generally well tolerated. The following adverse reactions have been reported in clinical trials.

Local Adverse Reactions

Pain at intravenous injection site – 3%
Thrombophlebitis – 3%
Phlebitis – 1.2%

Systemic Adverse Reactions

The most frequently reported adverse reactions were diarrhea in 3% of the patients and rash in less than 2% of the patients.

Additional systemic reactions reported in less than 1% of the patients were: itching, nausea, vomiting, candidiasis, fatigue, malaise, headache, chest pain, flatulence, abdominal distension, glossitis, urine retention, dysuria, edema, facial swelling, erythema, chills, tightness in throat, substernal pain, epistaxis and mucosal bleeding.

Pediatric Patients

Available safety data for pediatric patients treated with ampicillin and sulbactam demonstrate a similar adverse events profile to those observed in adult patients. Additionally, atypical lymphocytosis has been observed in one pediatric patient receiving ampicillin and sulbactam.

Adverse laboratory changes without regard to drug relationship that were reported during clinical trials were:

Hepatic: Increased AST (SGOT), ALT (SGPT), alkaline phosphatase, and LDH.
Hematologic: Decreased hemoglobin, hematocrit, RBC, WBC, neutrophils, lymphocytes, platelets and increased lymphocytes, monocytes, basophils, eosinophils, and platelets.
Blood Chemistry: Decreased serum albumin and total proteins.
Renal: Increased BUN and creatinine.
Urinalysis: Presence of RBC's and hyaline casts in urine.

Post-Marketing Experience

In addition to adverse reactions reported from clinical trials, the following have been identified during post-marketing use of ampicillin sodium and sulbactam sodium or other products containing ampicillin. Because they are reported voluntarily from a population of unknown size, estimates of frequency cannot be made. These events have been chosen for inclusion due to a combination of their seriousness, frequency, or potential causal connection to ampicillin sodium and sulbactam sodium.

Infections and Infestations: Clostridioides difficile-associated diarrhea (see WARNINGS section).

Blood and Lymphatic System Disorders: Hemolytic anemia, thrombocytopenic purpura, and agranulocytosis have been reported. These reactions are usually reversible on discontinuation of therapy and are believed to be hypersensitivity phenomena. Some individuals have developed positive direct Coombs Tests during treatment with ampicillin and sulbactam for injection, as with other beta-lactam antibacterials.

Gastrointestinal Disorders: Abdominal pain, cholestatic hepatitis, cholestasis, hyperbilirubinemia, jaundice, abnormal hepatic function, melena, gastritis, stomatitis, dyspepsia and black “hairy” tongue (see CONTRAINDICATIONS and WARNINGS sections).

General Disorders and Administration Site Conditions: Injection site reaction.

Immune System Disorders: Serious and fatal hypersensitivity (anaphylactic) reactions (see WARNINGS section). Acute myocardial ischemia with or without myocardial infarction may occur as part of an allergic reaction.

Metabolism and Nutrition Disorders: Hypokalemia

Nervous System Disorders: Convulsion and dizziness

Musculoskeletal and Connective Tissue Disorders: Arthralgia

Renal and Urinary Disorders: Tubulointerstitial nephritis

Respiratory, Thoracic and Mediastinal Disorders: Dyspnea

Skin and Subcutaneous Tissue Disorders: Toxic epidermal necrolysis, Stevens-Johnson syndrome, drug reaction with eosinophilia and systemic symptoms (DRESS), angioedema, Acute generalized exanthematous pustulosis (AGEP), erythema multiforme, exfoliative dermatitis, urticaria (see CONTRAINDICATIONS and WARNINGS sections), and linear IgA bullous dermatosis.

OVERDOSAGE

Neurological adverse reactions, including convulsions, may occur with the attainment of high CSF levels of beta-lactams. Ampicillin may be removed from circulation by hemodialysis. The molecular weight, degree of protein binding and pharmacokinetics profile of sulbactam suggest that this compound may also be removed by hemodialysis.

CLINICAL STUDIES

Skin and Skin Structure Infections in Pediatric Patients

Data from a controlled clinical trial conducted in pediatric patients provided evidence supporting the safety and efficacy of ampicillin and sulbactam for injection for the treatment of skin and skin structure infections. Of 99 pediatric patients evaluable for clinical efficacy, 60 patients received a regimen containing intravenous ampicillin and sulbactam, and 39 patients received a regimen containing intravenous cefuroxime. This trial demonstrated similar outcomes (assessed at an appropriate interval after discontinuation of all antimicrobial therapy) for ampicillin and sulbactam and cefuroxime-treated patients:

Table 2:

Therapeutic Regimen | Clinical Success | Clinical Failure
Ampicillin and Sulbactam | 51/60 (85%) | 9/60 (15%)
Cefuroxime | 34/39 (87%) | 5/39 (13%)

Most patients received a course of oral antimicrobials following initial treatment with intravenous administration of parenteral antimicrobials. The study protocol required that the following three criteria be met prior to transition from intravenous to oral antimicrobial therapy: (1) receipt of a minimum of 72 hours of intravenous therapy; (2) no documented fever for prior 24 hours; and (3) improvement or resolution of the signs and symptoms of infection.

The choice of oral antimicrobial agent used in this trial was determined by susceptibility testing of the original pathogen, if isolated, to oral agents available. The course of oral antimicrobial therapy should not routinely exceed 14 days.

DOSAGE AND ADMINISTRATION

Ampicillin and sulbactam for injection is administered intravenously.

For intravenous administration, the dose can be given by slow intravenous injection over at least 10 to 15 minutes or can also be delivered in greater dilutions with 50 mL to 100 mL of a compatible diluent as an intravenous infusion over 15 to 30 minutes. (see DIRECTION FOR USE-Preparation of Intravenous Use section)

The recommended adult dosage of ampicillin and sulbactam for injection is 1.5 g (ampicillin 1g and sulbactam 0.5 g) to 3 g (ampicillin 2 g and sulbactam 1 g) every six hours. This 1.5 g to 3 g range represents the total of ampicillin content plus the sulbactam content of ampicillin and sulbactam for injection and corresponds to a range of 1 g ampicillin and 0.5 g sulbactam to 2 g ampicillin and 1 g sulbactam. The total dose of sulbactam should not exceed 4 g per day.

Pediatric Patients 1 Year of Age or Older

The recommended daily dose of ampicillin and sulbactam for injection in pediatric patients is 300 mg per kg of body weight administered via intravenous infusion in equally divided doses every 6 hours. This 300 mg/kg/day dosage represents the total ampicillin content plus the sulbactam content of ampicillin and sulbactam for injection and corresponds to 200 mg ampicillin and 100 mg sulbactam per kg per day. Pediatric patients weighing 40 kg or more should be dosed according to adult recommendations, and the total dose of sulbactam should not exceed 4 g per day. The course of intravenous therapy should not routinely exceed 14 days. In clinical trials, most pediatric patients received a course of oral antimicrobials following initial treatment with intravenous ampicillin and sulbactam for injection (see CLINICAL STUDIES section).

Impaired Renal Function

In patients with impairment of renal function the elimination kinetics of ampicillin and sulbactam are similarly affected, hence the ratio of one to the other will remain constant whatever the renal function.

The dose of ampicillin and sulbactam for injection in such patients should be administered less frequently in accordance with the usual practice for ampicillin and according to the following recommendations:

TABLE 3: Ampicillin and Sulbactam for Injection Dosage Guide for Patients with Renal Impairment

Creatinine Clearance (mL/min/1.73m^2) | Ampicillin and Sulbactam Half-Life (Hours) | Recommended Ampicillin and Sulbactam for Injection Dosage
≥ 30 | 1 | 1.5 g to 3 g every 6 to 8 hours
15 to 29 | 5 | 1.5 g to 3 g every 12 hours
5 to 14 | 9 | 1.5 g to 3 g every 24 hours

When only serum creatinine is available, the following formula (based on sex, weight, and age of the patient) may be used to convert this value into creatinine clearance. The serum creatinine should represent a steady state of renal function.

Males | weight (kg) x (140 - age)
 | 72 x serum creatinine
Females | 0.85 x above value

COMPATIBILITY, RECONSTITUTION AND STABILITY

Ampicillin and sulbactam for injection sterile powder is to be stored at 20°C to 25°C (68°F to 77°F) [see USP Controlled Room Temperature] prior to reconstitution.

When concomitant therapy with aminoglycosides is indicated, ampicillin and sulbactam and aminoglycosides should be reconstituted and administered separately, due to the in vitro inactivation of aminoglycosides by any of the aminopenicillins.

DIRECTIONS FOR USE

1.5 g ADD-Vantage® Vials: Ampicillin and sulbactam for injection in the ADD-Vantage® system is intended as a single dose for intravenous administration after dilution with the ADD-Vantage® Flexible Diluent Container containing 50 mL, 100 mL or 250 mL of 0.9% Sodium Chloride Injection, USP.

3 g ADD-Vantage® Vials: Ampicillin and sulbactam for injection in the ADD-Vantage® system is intended as a single dose for intravenous administration after dilution with the ADD-Vantage® Flexible Diluent Container containing 100 mL or 250 mL of 0.9% Sodium Chloride Injection, USP.

Ampicillin and sulbactam for injection in the ADD-Vantage® system is to be reconstituted with 0.9% Sodium Chloride Injection, USP only. See INSTRUCTIONS FOR USE OF THE ADD-Vantage® VIAL section. Reconstitution of ampicillin and sulbactam for injection, at the specified concentration, with 0.9% Sodium Chloride Injection, USP provides stable solutions for the time period indicated below:

Table 5:

Diluent | Maximum Concentration (mg/mL) Ampicillin and Sulbactam | Use Period
0.9% Sodium Chloride Injection, USP | 30 (20/10) | 8 hours at 25°C

In 0.9% Sodium Chloride Injection, USP

The final diluted solution of ampicillin and sulbactam for injection should be completely administered within 8 hours in order to assure proper potency.

Animal Pharmacology

While reversible glycogenosis was observed in laboratory animals, this phenomenon was dose- and time-dependent and is not expected to develop at the therapeutic doses and corresponding plasma levels attained during the relatively short periods of combined ampicillin sodium and sulbactam sodium therapy in man.

HOW SUPPLIED

Ampicillin and Sulbactam for Injection, USP (ampicillin sodium/sulbactam sodium) is supplied as a sterile white to yellowish dry powder in ADD-Vantage® Vials as follows:

Each 1.5 grams ADD-Vantage® vial contains 1.5 g Ampicillin and Sulbactam for Injection, USP (equivalent to 1 g ampicillin as the sodium salt plus 0.5 g sulbactam as the sodium salt).

NDC 0409-2689-01-packed in trays of 10 vials.

Each 3 grams ADD-Vantage® vial contains 3 g Ampicillin and Sulbactam for Injection, USP (equivalent to 2 g ampicillin as the sodium salt plus 1 g sulbactam as the sodium salt).

NDC 0409-2987-03-packed in trays of 10 vials.

The 1.5 g Ampicillin and Sulbactam for Injection, USP ADD-Vantage® vials are only to be used with an ADD-Vantage® Flexible Diluent Container containing 0.9% Sodium Chloride Injection, USP, 50 mL, 100 mL or 250 mL sizes.

The 3 g Ampicillin and Sulbactam for Injection, USP ADD-Vantage® vials are only to be used with an ADD-Vantage® Flexible Diluent Container containing 0.9% Sodium Chloride Injection, USP, 100 mL or 250 mL sizes.

STORAGE AND HANDLING

Ampicillin and Sulbactam for Injection, USP sterile powder is to be stored at 20°C to 25°C (68°F to 77°F) [see USP Controlled Room Temperature] prior to reconstitution.

ADD-Vantage® is a registered trademark of Hospira, Inc.

INSTRUCTIONS FOR USE OF THE ADD-Vantage® VIAL

To Open Diluent Container: Peel overwrap from the corner and remove container. Some opacity of the plastic due to moisture absorption during the sterilization process may be observed. This is normal and does not affect the solution quality or safety. The opacity will diminish gradually.

To Assemble Vial and Flexible Diluent Container: (Use Aseptic Technique)

1. Remove the protective covers from the top of the vial and the vial port on the diluent container as follows:
  a. To remove the breakaway vial cap, swing the pull ring over the top of the vial and pull down far enough to start the opening (see Figure 1), pull the ring approximately half way around the cap and then pull straight up to remove the cap (see Figure 2).
NOTE: Do not access vial with syringe.
b. To remove the vial port cover, grasp the tab on the pull ring, pull up to break the three tie strings, then pull back to remove the cover (see Figure 3).
2. Screw the vial into the vial port until it will go no further. THE VIAL MUST BE SCREWED IN TIGHTLY TO ASSURE A SEAL. This occurs approximately 1/2 turn (180°) after the first audible click (see Figure 4). The clicking sound does not assure a seal, the vial must be turned as far as it will go. NOTE: Once vial is sealed, do not attempt to remove (see Figure 4).
3. Recheck the vial to assure that it is tight by trying to turn it further in the direction of assembly.
4. Label appropriately.

To Prepare Admixture

1. Squeeze the bottom of the diluent container gently to inflate the portion of the container surrounding the end of the drug vial.
2. With the other hand, push the drug vial down into the container telescoping the walls of the container. Grasp the inner cap of the vial through the walls of the container (see Figure 5).
3. Pull the inner cap from the drug vial (see Figure 6). Verify that the rubber stopper has been pulled out, allowing the drug and diluent to mix.
4. Mix container contents thoroughly and use within the specified time.

To report SUSPECTED ADVERSE EVENTS, contact Hospira, Inc. at 1-800-441-4100 or FDA at 1-800-FDA-1088 or http://www.fda.gov/medwatch for voluntary reporting of adverse reactions.

Revised: 12/2025

Manufactured by Sandoz GmbH for

Hospira, Inc., Lake Forest, IL 60045, USA

1.5 gram Label

NDC 0409-2689-01 Rx only

Ampicillin and

Sulbactam for

Injection, USP

1.5 grams

Sterile For I.V. use only

equivalent to 1 g of ampicillin plus

0.5 g of sulbactam

10 Single-Dose

ADD-Vantage® Vial

Hospira

3 gram Label

NDC 0409-2987-03 Rx only

Ampicillin and

Sulbactam for

Injection, USP

3 grams

Sterile For I.V. use only

equivalent to 2 g of ampicillin plus

1 g of sulbactam

10 Single Dose

ADD-Vantage® Vial

Hospira